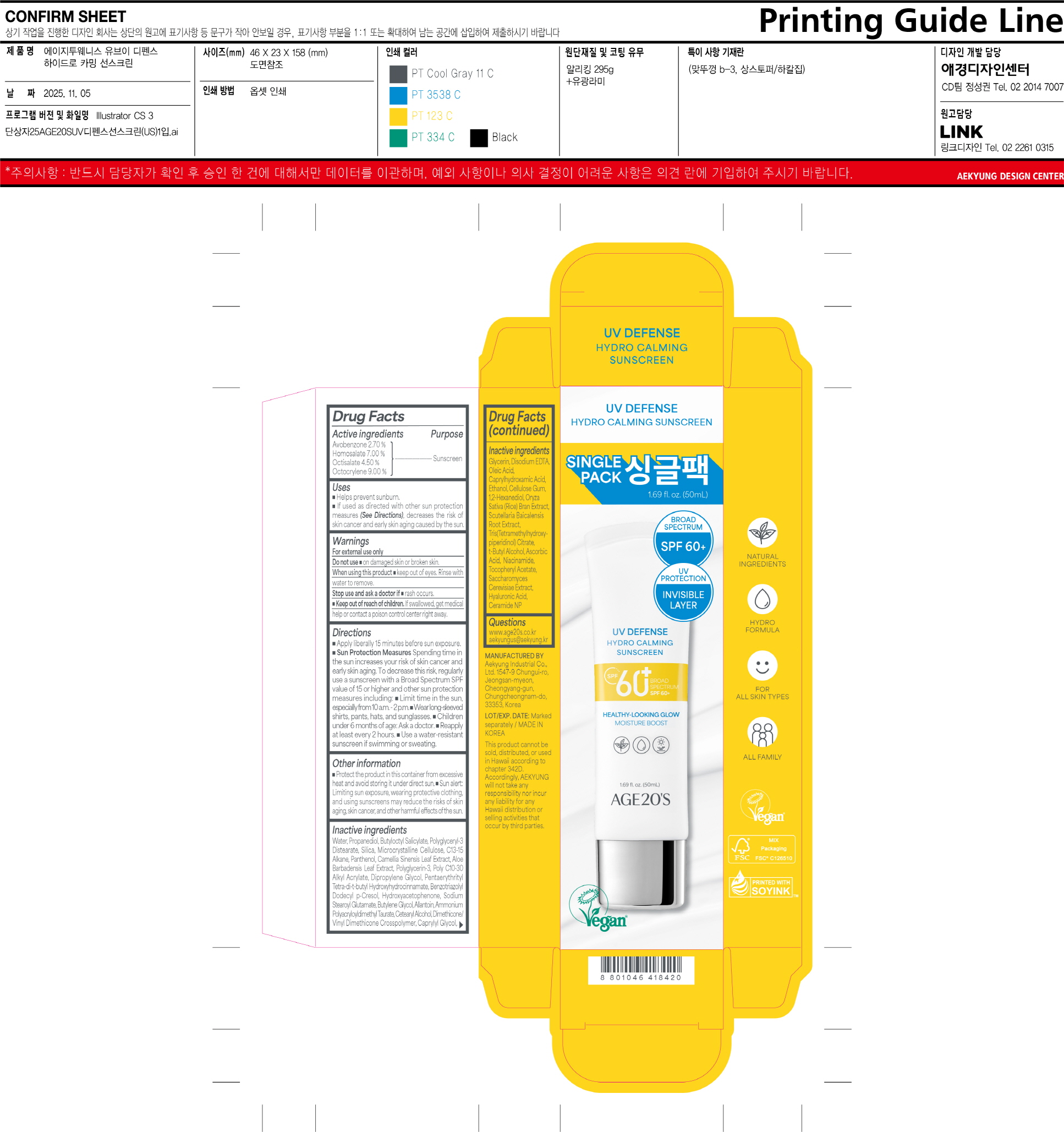 DRUG LABEL: AGE20S UV DEFENSE HYDRO CALMING SUNSCREEN
NDC: 67225-5033 | Form: CREAM
Manufacturer: Aekyung Industrial Co., Ltd.
Category: otc | Type: HUMAN OTC DRUG LABEL
Date: 20251209

ACTIVE INGREDIENTS: AVOBENZONE 1.35 g/50 g; OCTISALATE 2.25 g/50 g; OCTOCRYLENE 4.5 g/50 g; HOMOSALATE 3.5 g/50 g
INACTIVE INGREDIENTS: PANTHENOL; PENTAERYTHRITOL TETRAKIS(3-(3,5-DI-TERT-BUTYL-4-HYDROXYPHENYL)PROPIONATE); BUTYLENE GLYCOL; ALLANTOIN; TRIS(TETRAMETHYLHYDROXYPIPERIDINOL) CITRATE; ASCORBIC ACID; WATER; ALOE VERA LEAF; SODIUM STEAROYL GLUTAMATE; PROPANEDIOL; GREEN TEA LEAF; POLYGLYCERIN-3; BENZOTRIAZOLYL DODECYL P-CRESOL; HYDROXYACETOPHENONE; SCUTELLARIA BAICALENSIS ROOT; DIPROPYLENE GLYCOL; 1,2-HEXANEDIOL; EDETATE DISODIUM; MICROCRYSTALLINE CELLULOSE; BEHENYL ACRYLATE POLYMER; CARBOXYMETHYLCELLULOSE SODIUM; CETOSTEARYL ALCOHOL; DIMETHICONE/VINYL DIMETHICONE CROSSPOLYMER (SOFT PARTICLE); BUTYLOCTYL SALICYLATE; RICE BRAN; TERT-BUTYL ALCOHOL; HYALURONIC ACID; POLYGLYCERYL-3 DISTEARATE; GLYCERIN; NIACINAMIDE; SACCHAROMYCES CEREVISIAE; OLEIC ACID; SILICON DIOXIDE; CAPRYLHYDROXAMIC ACID; ALCOHOL; C13-15 ALKANE; AMMONIUM POLYACRYLOYLDIMETHYL TAURATE; CAPRYLYL GLYCOL; .ALPHA.-TOCOPHEROL ACETATE; CERAMIDE NP

67225-5033 AGE20S UV DEFENSE HYDRO CALMING SUNSCREEN

ACTIVE INGREDIENT

Avobenzone 2.70%

Homosalate 7.00%

Octisalate 4.50%

Octocrylene 9.00%

PURPOSE

Sunscreen

INDICATIONS AND USAGE

■ Helps prevent sunburn.

■ If used as directed with other sun protection measures (See Directions), decreases the risk of skin cancer and early skin aging caused by the sun.

WARNINGS

For external use only

DO NOT USE

■ damaged skin or broken skin

WHEN USING

this product ■ keep out of eyes. Rinse with water to remove.

STOP USE

and ask a doctorif ■ rash occurs.

KEEP OUT OF REACH OF CHILDREN

If swallowed, get medical help or contact poison control center right away.

INACTIVE INGREDIENT

Water, Propanediol, Butyloctyl Salicylate, Polyglyceryl-3 Distearate, Silica, Microcrystalline Cellulose, C13-15 Alkane, Panthenol, Camellia Sinensis Leaf Extract, Aloe Barbadensis Leaf Extract, Polyglycerin-3, Poly C10-30 Alkyl Acrylate, Dipropylene Glycol, Pentaerythrityl Tetra-di-t-butyl Hydroxyhydrocinnamate, Benzotriazolyl Dodecyl p-Cresol, Hydroxyacetophenone, Sodium Stearoyl Glutamate, Butylene Glycol, Allantoin, Ammonium Polyacryloyldimethyl Taurate, Cetearyl Alcohol, Dimethicone/Vinyl Dimethicone Crosspolymer, Caprylyl Glycol, Glycerin, Disodium EDTA, Oleic Acid, Caprylhydroxamic Acid, Ethanol, Cellulose Gum, 1,2-Hexanediol, Oryza Sativa (Rice) Bran Extract, Scutellaria Baicalenesis Root Extract, Tris(Tetramethylhy- droxypiperidinol) Citrate, t-Butyl Alcohol, Ascorbic Acid, Niacinamide, Tocopheryl Acetate, Saccharomyces Cerevisiae Extract, Hyaluronic Acid, Ceramide NP

OTHER SAFETY INFORMATION

■ Protect the product in the container from excessive heat and avoid storing it under direct sun.

■ Sun alert: Limiting sun exposure, wearing protective clothing, and using sunscreens may reduce the risks of skin aging, skin cancer, and other harmful effects of the sun.

Directions

■ Apply liberally 15 minutes before sun exposure.

■ Children under 6 months of age: Ask a doctor.

■ Reapply at least every 2 hours.

■ Use a water-resistant sunscreen if swimming or sweating

■ Sun Protection Measures. Spending time in the sun increases your risk of skin cancer and early skin aging. Todecrease this risk, regularly use a sunscreen with a Broad Spectrum SPF value of 15 or higher and other sun protection measures including:

■ Limit time in the sun, especially from 10 a.m. - 2 p.m.

■ Wear long-sleeved shirts, pants, hats, and sunglasses.